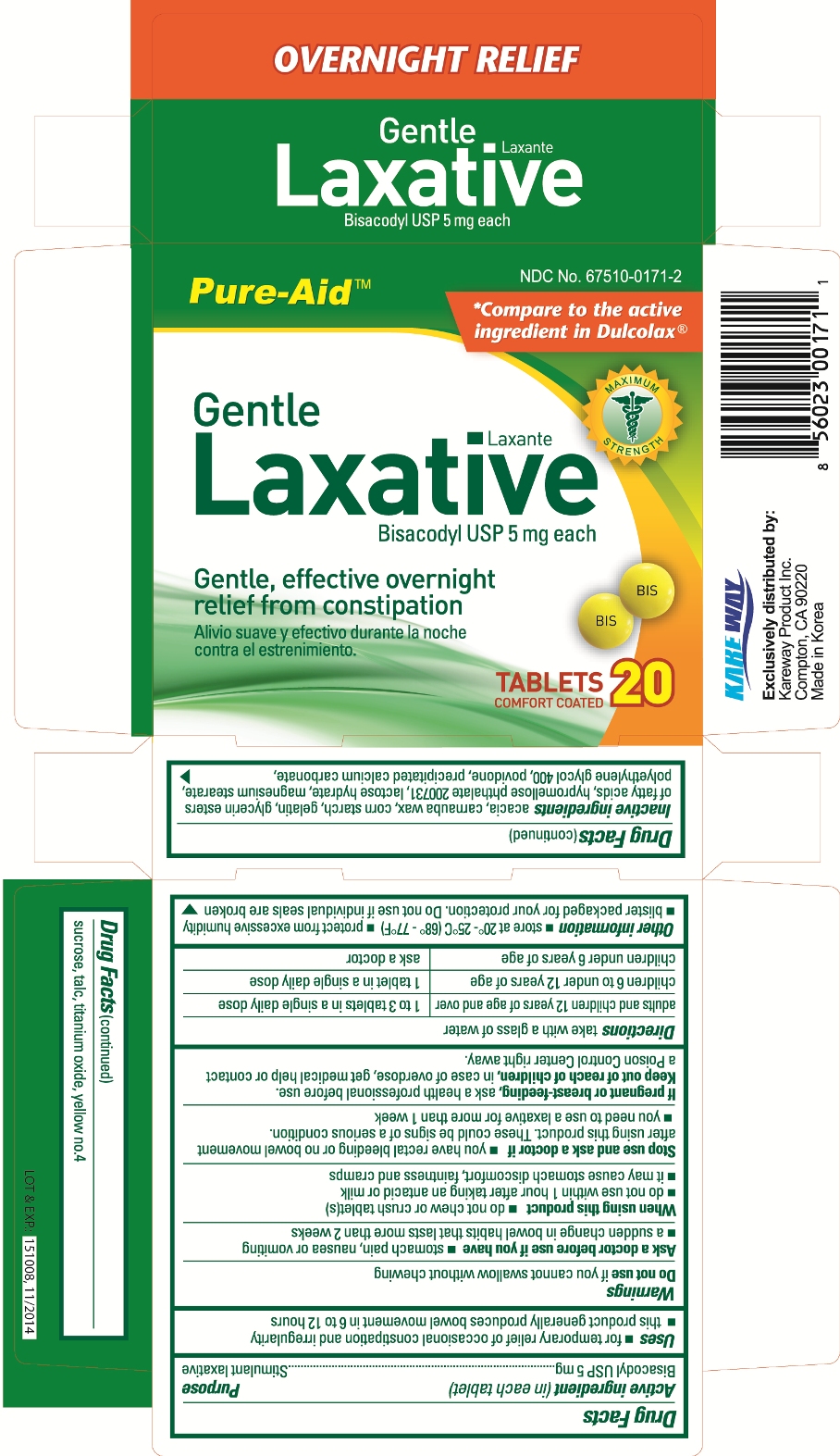 DRUG LABEL: Gentle Laxative
NDC: 67510-0171 | Form: TABLET, COATED
Manufacturer: Kareway Product, Inc.
Category: otc | Type: HUMAN OTC DRUG LABEL
Date: 20120215

ACTIVE INGREDIENTS: BISACODYL 5 mg/1 1
INACTIVE INGREDIENTS: ACACIA; CARNAUBA WAX; STARCH, CORN; GELATIN; HYPROMELLOSE PHTHALATE (24% PHTHALATE, 55 CST); LACTOSE MONOHYDRATE; MAGNESIUM STEARATE; POLYETHYLENE GLYCOL 400; POVIDONE; CALCIUM CARBONATE; SUCROSE; TALC; TITANIUM DIOXIDE

Drug facts

Active ingredient (in each tablet)

Bisacodyl USP 5 mg

Purpose

Stimulant laxative

Uses

- for temporary relief of occasional constipation and irregularity
- this product generally produces bowel movement in 6 to 12 hours

Warnings

Do not use if you cannot swallow without chewing

Ask a doctor before use if you have

- stomach pain, nausea or vomiting
- a sudden change in bowel habits that lasts more than 2 weeks

When using this product

- do not chew or crush tablet(s)
- do not use within 1 hour after taking an antacid or milk
- it may cause stomach discomfort, faintness and cramps

Stop use and ask a doctor if

- you have rectal bleeding or no bowel movement after using this product. These could be signs of a serious condition.
- you need to use a laxative for more than 1 week

If pregnant or breast-feeding,

ask a health professional before use.

Keep out of reach of children,

in case of overdose, get medical help or contact a Poison Control Center right away.

Directions

take with a glass of water

adults and children 12 years of age and over | 1 to 3 tablets in a single daily dose
children 6 to under 12 years of age | 1 tablet in a single daily dose
children under 6 years of age | ask a doctor

Other information

- store at 20° - 25°C (68° - 77°F)
- protect from excessive humidity
- blister packaged for your protection. Do not use if individual seals are broken.

Inactive ingredients

acacia, carnauba wax, corn starch, gelatin, glycerin esters of fatty acids, hypromellose phthalate 200731, lactose hydrate, magnesium stearate, polyethylene glycol 400, povidone, precipitated calcium carbonate, sucrose, talc, titanium oxide, yellow no. 4

Package label

Gentle Laxative